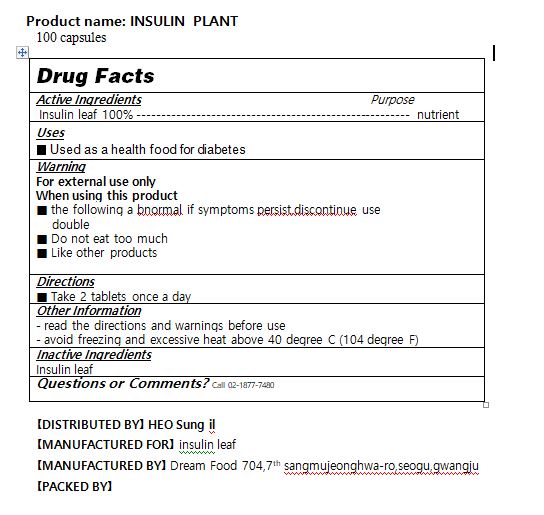 DRUG LABEL: INSULIN PLANT
NDC: 79831-0001 | Form: CAPSULE
Manufacturer: Dream Food
Category: otc | Type: HUMAN OTC DRUG LABEL
Date: 20200727

ACTIVE INGREDIENTS: CINNAMOMUM CAMPHORA LEAF 250 1/1 1
INACTIVE INGREDIENTS: DIFLUBENZURON

ACTIVE INGREDIENT

insulin leaf

INACTIVE INGREDIENT

diflubenzuron

PURPOSE

Treatment and prevention of osteoporosis

Growth and development

Treatment and prediction of cardiovascular disease due to calcification of blood

Attention deficit in children, depression, nervous symptoms, nervous stability to anxiety

Myalgia, Bone Pain, Arthritis, Dysmenorrhea Treatment

KEEP OUT OF REACH OF CHILDREN

WARNING

Please check product ingredients if you have any allergies before taking.

Please be careful during open the product package.

Keep product out of direct sunlight, high temperature and humidity.

Store in a cool dry place.

Any items past the expiration date or damaged in transit can be exchanged where you originally purchased the item.

consult your doctor if any abnormal symptoms occur

USES

for diabetes

INDICATION & USAGE SECTION

Take 2 tablets once a day